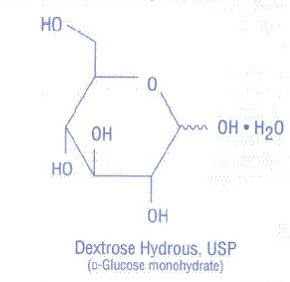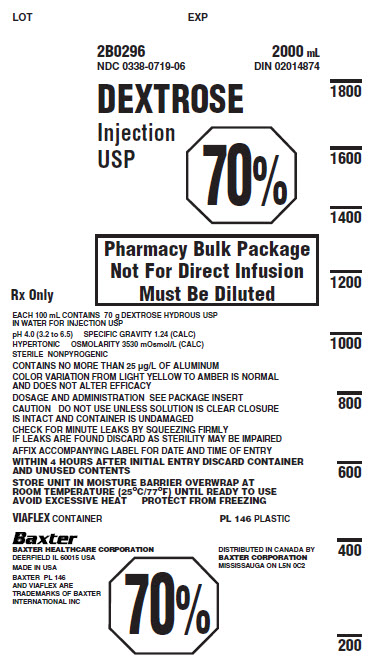 DRUG LABEL: DEXTROSE
NDC: 0338-0719 | Form: INJECTION, SOLUTION
Manufacturer: Baxter Healthcare Corporation
Category: prescription | Type: HUMAN PRESCRIPTION DRUG LABEL
Date: 20190805

ACTIVE INGREDIENTS: DEXTROSE MONOHYDRATE 70 g/100 mL
INACTIVE INGREDIENTS: Water

HIGHLIGHTS OF PRESCRIBING INFORMATION

These highlights do not include all the information needed to use DEXTROSE INJECTION 70% safely and effectively. See full prescribing information for DEXTROSE INJECTION 70%.
DEXTROSE injection, for intravenous use
Initial U.S. Approval: 1940

1 INDICATIONS AND USAGE

Dextrose Injection is indicated as a source of calories when mixed with amino acids or other compatible intravenous fluids for patients requiring parenteral nutrition when oral or enteral nutrition is not possible, insufficient or contraindicated. (1)

2 DOSAGE AND ADMINISTRATION

- Pharmacy Bulk Package. Not for direct intravenous infusion. (2.1)
- For slow intravenous infusion only into a: (2.2)
- Central vein, if final dextrose concentration is greater than 5% or osmolality is greater than 900 mOsm/L approximately.
- Peripheral vein, if final dextrose concentration 5% or less and osmolality is less than 900 mOsm/L approximately.
- Individualize dosage based on the patient’s clinical condition, body weight, nutritional/fluid requirements, as well as additional energy given orally/enterally. (2.3)
- Discontinue infusion of concentrated dextrose solutions slowly. (2.4)

3 DOSAGE FORMS AND STRENGTHS

- Injection: 70% (0.7 grams/mL), 70 grams of dextrose hydrous per 100 mL in a 2000 mL Pharmacy Bulk Package flexible container. (3)

4 CONTRAINDICATIONS

Severe dehydration. (4)

5 WARNINGS AND PRECAUTIONS

- Pulmonary Embolism due to Pulmonary Vascular Precipitates: If signs of pulmonary distress occur, stop the infusion and initiate a medical evaluation. (5.1)
- Hyperglycemia or Hyperosmolar Hyperglycemic State: Monitor blood glucose and administer insulin as needed. (5.2)
- Hypersensitivity Reactions: Monitor for signs and symptoms and discontinue infusion if reactions occur. (5.3)
- Vein Damage and Thrombosis: Administer solutions containing more than 5% dextrose as the final concentration or solutions with an osmolarity of approximately 900 mOsm/L or greater through a central vein. (2.2, 5.4)
- Hyponatremia: Monitor serum sodium to minimize the risk of hypo- or hyperosmotic hyponatremia. (5.5)
- Risk of Infection: Monitor for signs and symptoms and laboratory parameters. (5.6)
- Refeeding Syndrome: Monitory laboratory parameters. (5.7)
- Hepatobiliary Disorders: Monitor liver function parameters and ammonia levels. (5.8)
- Aluminum Toxicity: Dextrose Injection contains aluminum that may be toxic. Adult patients with impaired renal function and preterm infants are at higher risk. Limit aluminum to less than 4 mcg/kg/day (5.9, 8.4)
- Parenteral Nutrition Associated Liver Disease: Increased risk in patients who receive parenteral nutrition for extended periods of time, especially preterm infants; monitor liver function tests, if abnormalities occur consider discontinuation or dosage reduction. (5.10, 8.4)
- Electrolyte Imbalance and Fluid Overload: Monitor daily fluid balance, blood electrolyte levels, correct as needed. (5.11, 8.4)

6 ADVERSE REACTIONS

The most common adverse reactions are, hyperglycemia, hypersensitivity reactions, infection both systemic and at the injection site, and vein thrombosis or phlebitis. (6)

To report SUSPECTED ADVERSE REACTIONS, contact Baxter Healthcare at 1-866-888-2472 or FDA at 1-800-FDA-1088 or www.fda.gov/medwatch.

7 DRUG INTERACTIONS

Other Products that Affect Glycemic Control, Vasopressin or Fluid and/or Electrolyte Balance: Monitor blood glucose concentrations, fluid balance serum electrolyte concentrations and acid-base balance. (7.1)

8 USE IN SPECIFIC POPULATIONS

Pediatric Use: Increased risk of hypoglycemia/hyperglycemia; monitor serum glucose concentrations. (8.4)

FULL PRESCRIBING INFORMATION

1 INDICATIONS AND USAGE

Dextrose Injection is indicated as source of calories and fluid replenishment when mixed with amino acids or other compatible intravenous fluids for patients requiring parenteral nutrition (PN) when oral or enteral nutrition is not possible, insufficient or contraindicated.

2 DOSAGE AND ADMINISTRATION

2.1 Preparation Instructions Prior to Administration

Dextrose Injection is supplied as a pharmacy bulk package for admixing only and is not for direct intravenous infusion. Dextrose Injection is intended for use in the preparation of sterile, intravenous admixtures. Prior to administration, Dextrose Injection must be transferred to a separate PN container, diluted with other compatible intravenous fluids and used as an admixture in PN solutions.

- Do not remove from overpouch until ready to use.
- Tear protective overwrap at slit and remove solution container. Small amounts of moisture may be found on the solution container from water permeating from inside the container. The amount of permeated water is insufficient to affect the solution significantly. If larger amounts of water are found, the container should be checked for tears or leaks.
- Inspect Dextrose Injection prior to use. Opacity of the container may be observed due to moisture absorption during the sterilization process. This is normal and does not affect the solution quality or safety. The opacity will diminish gradually. Evaluate the following:
  - If the outlet port protector is damaged, detached, or not present, discard container as solution path sterility may be impaired.
  - Check for minute leaks by squeezing the inner container firmly. If leaks are found, discard solution as sterility may be impaired.
  - Do not use unless solution is clear and container is intact.
- Because additives may be incompatible, evaluate all additions for compatibility and stability of the resulting preparation. Consult with a pharmacist, if available. If it is deemed advisable to introduce additives, use aseptic technique and mix thoroughly.
- Calcium and phosphate ratios must be considered. Excess addition of calcium and phosphate, especially in the form of mineral salts, may result in the formation of calcium phosphate precipitates [see Warnings and Precautions (5.1)].

Preparation for Admixing

1. The Pharmacy Bulk Package is to be used only in a suitable work area such as a laminar flow hood (or an equivalent clean air compounding area).
2. Suspend container from eyelet support.
3. Remove plastic protector from outlet port at bottom of container.
4. Attach solution transfer set. Refer to complete directions accompanying set.
  Note: The closure shall be penetrated only one time with a suitable sterile transfer device or dispensing set which allows measured dispensing of the contents.
5. The VIAFLEX plastic container should not be written on directly since ink migration has not been investigated. Affix accompanying label for date and time of entry notation.
6. Once container closure has been penetrated, withdrawal of contents should be completed without delay. After initial entry, maintain contents at room temperature (25°C/77°F) and dispense within 4 hours.

2.2 Important Administration Instructions

- Dextrose Injection is for admixing use only and is not for direct intravenous infusion. Prior to administration, Dextrose Injection must be diluted with other compatible intravenous fluids and used as an admixture in PN solutions.
- To prevent air embolism, use a non-vented infusion set or close the vent on a vented set, avoid multiple connections, do not connect flexible containers in series, fully evacuate residual gas in the container prior to administration, do not pressurize the flexible container to increase flow rates, and if administration is controlled by a pumping device, turn off pump before the container runs dry.
- When Dextrose Injection is admixed, the choice of a central or peripheral venous route should depend on the osmolarity of the final infusate. Solutions with an osmolarity of 900 mOsm/L or greater must be infused through a central venous catheter [see Warnings and Precautions (5.4)].
- Prior to infusion, visually inspect the PN solution to ensure precipitates have not formed during the mixing or addition of additives. Discard container if precipitates are observed.
- If admixed or infused with lipid emulsion, do not use administration sets and lines that contain di-2-ethylhexyl phthalate (DEHP). Administration sets that contain polyvinyl chloride (PVC) components have DEHP as a plasticizer.

2.3 Dosing Instructions

Caution: Dextrose Injection is not for direct intravenous infusion. Prior to administration, Dextrose Injection must be diluted with other compatible intravenous fluids or used as an admixture in PN solutions.

Dextrose Injection is a part of the parenteral nutrition (PN) regimen which also includes amino acids, electrolytes, and possibly lipid emulsion. Protein, caloric, fluid and electrolyte requirements all need to be taken into consideration when determining individual patient dosage needs.

Individualize the dosage of Dextrose Injection based on the patient’s clinical condition (ability to adequately metabolize dextrose), body weight, nutritional and fluid requirements, as well as additional energy given orally or enterally to the patient. Vitamins and trace elements and other components (including amino acids, electrolytes, and lipid emulsion) can be added to the PN solution to meet nutrient needs and prevent deficiencies and complications from developing.

The administration rate should be governed, especially during the first few days of therapy, based on the patient’s tolerance to dextrose. Daily intake of amino acids and dextrose should be increased gradually to the maximum required dose as indicated by frequent determinations of blood glucose levels.

In many patients, provision of adequate calories in the form of hypertonic dextrose may require the administration of exogenous insulin to prevent hyperglycemia and glycosuria.

2.4 Discontinuation of Dextrose Injection

To reduce the risk of hypoglycemia, a gradual decrease in flow rate in the last hour of infusion should be considered [see Warnings and Precautions (5.2), Use in Specific Populations (8.4)].

3 DOSAGE FORMS AND STRENGTHS

Dextrose Injection 70%, USP is a sterile, non-pyrogenic, hypertonic solution of 70 grams of dextrose hydrous per 100 mL (0.7 grams/mL) in a 2000 mL Pharmacy Bulk Package flexible container.

4 CONTRAINDICATIONS

The use of Dextrose Injection is contraindicated in patients:

- Who are severely dehydrated as hypertonic dextrose solution can worsen the patient’s hyperosmolar state [see Warnings and Precautions (5.2)].
- Known hypersensitivity to dextrose [see Warnings and Precautions (5.3)].

5 WARNINGS AND PRECAUTIONS

5.1 Pulmonary Embolism due to Pulmonary Vascular Precipitates

Pulmonary vascular precipitates causing pulmonary vascular emboli and pulmonary distress have been reported in patients receiving parenteral nutrition. In some cases, fatal outcomes due to pulmonary embolism have occurred. Patients, especially those with hypophosphatemia, may require the addition of phosphate. To prevent hypocalcemia, calcium supplementation should always accompany phosphate administration. Excessive addition of calcium and phosphate increases the risk of the formation of calcium phosphate precipitates. Precipitates have been reported even in the absence of phosphate salt in the solution. Precipitation following passage through an in-line filter and suspected in vivo precipitate formation has also been reported. If signs of pulmonary distress occur, stop the infusion and initiate a medical evaluation. In addition to inspection of the solution [see Dosage and Administration (2.1, 2.2)], the infusion set and catheter should also periodically be checked for precipitates.

5.2 Hyperglycemia and Hyperosmolar Hyperglycemic State

The use of dextrose infusions in patients with impaired glucose tolerance may worsen hyperglycemia. Administration of dextrose at a rate exceeding the patient’s utilization rate may lead to hyperglycemia, coma, and death.

Hyperglycemia is associated with an increase in serum osmolality, resulting in osmotic diuresis, dehydration and electrolyte losses [see Warnings and Precautions (5.11)]. Patients with underlying CNS disease and renal impairment who receive dextrose infusions, may be at greater risk of developing hyperosmolar hyperglycemic state.

Monitor blood glucose levels and treat hyperglycemia to maintain levels within normal limits while administering Dextrose Injection. Insulin may be administered or adjusted to maintain optimal blood glucose levels during Dextrose Injection administration.

5.3 Hypersensitivity Reactions

Hypersensitivity and infusion reactions including anaphylaxis have been reported with dextrose injection [see Adverse Reactions (6)]. Stop infusion immediately and treat patient accordingly if signs or symptoms of a hypersensitivity reaction develop. Signs or symptoms may include: pruritis, bronchospasm, cyanosis, angioedema, hypotension, pyrexia, chills, and rash.

5.4 Vein Damage and Thrombosis

Dextrose Injection is for admixture with amino acids or dilution with other compatible intravenous fluids. It is not for direct intravenous infusion. Administer solutions with an osmolarity of ≥ 900 mOsm/L through a central vein [see Dosage and Administration (2.2)]. The infusion of hypertonic solutions into a peripheral vein may result in vein irritation, vein damage, and/or thrombosis. The primary complication of peripheral access is venous thrombophlebitis, which manifests as pain, erythema, tenderness or a palpable cord. Remove the catheter as soon as possible, if thrombophlebitis develops.

5.5 Hyponatremia

Dextrose Injection is a hypertonic solution [see Description, Table 1 (11)]. In the body, however, glucose containing fluids can become extremely physiologically hypotonic due to rapid glucose metabolization. Monitoring of serum sodium is particularly important for hypotonic fluids.

Depending on the tonicity of the solution, the volume and rate of infusion, and depending on a patient’s underlying clinical condition and capability to metabolize glucose, intravenous administration of glucose can cause electrolyte disturbances, most importantly hypo- or hyperosmotic hyponatremia.

The risk for hyponatremia is increased, in pediatric patients, elderly patients, postoperative patients, those with psychogenic polydipsia and in patients treated with medications that increase the risk of hyponatremia (such as certain diuretic, antiepileptic and psychotropic medications). Close clinical monitoring may be warranted.

Acute hyponatremia can lead to acute hyponatremic encephalopathy characterized by headache, nausea, seizures, lethargy and vomiting. Patients with brain edema are at particular risk of severe, irreversible and life-threatening brain injury. Patients at increased risk for developing complications of hyponatremia, such as hyponatremic encephalopathy include pediatric patients; women, in particular, premenopausal women; patients with hypoxemia; and in patients with underlying central nervous system disease [see Use in Specific Populations (8.4)].

Rapid correction of hyponatremia is potentially dangerous with risk of serious neurologic complications such as osmotic demyelination syndrome with risk of seizures and cerebral edema. To avoid complications, monitor serum sodium and chloride concentrations, fluid status, acid-base balance, and signs of neurologic complications.

High volume infusion must be used with close monitoring in patients with cardiac or pulmonary failure, and in patients with non-osmotic vasopressin release (including SIADH), due to the risk of hospital-acquired hyponatremia.

5.6 Risk of Infections

Patients who require parenteral nutrition are at high risk of infections because the nutritional components of these solutions can support microbial growth. Infection and sepsis may also occur as a result of the use of intravenous catheters to administer parenteral nutrition.

The risk of infection is increased in patients with malnutrition-associated immunosuppression, hyperglycemia exacerbated by dextrose infusion, long-term use and poor maintenance of intravenous catheters, or immunosuppressive effects of other concomitant conditions, drugs, or other components of the parenteral formulation (e.g., lipid emulsion).

To decrease the risk of infectious complications, ensure aseptic technique in catheter placement and maintenance, as well as aseptic technique in the preparation and administration of the nutritional formula.

Monitor for signs and symptoms (including fever and chills) of early infections, including laboratory test results (including leukocytosis and hyperglycemia) and frequent checks of the parenteral access device and insertion site for edema, redness and discharge.

5.7 Refeeding Syndrome

Refeeding severely undernourished patients may result in refeeding syndrome, characterized by the intracellular shift of potassium, phosphorus, and magnesium as the patient becomes anabolic. Thiamine deficiency and fluid retention may also develop. To prevent these complications, monitor severely undernourished patients and slowly increase nutrient intakes including Dextrose Injection.

5.8 Hepatobiliary Disorders

Hepatobiliary disorders are known to develop in some patients without preexisting liver disease who receive parenteral nutrition, including cholecystitis, cholelithiasis, cholestasis, hepatic steatosis, fibrosis and cirrhosis, possibly leading to hepatic failure. The etiology of these disorders is thought to be multifactorial and may differ between patients.

Monitor liver function parameters and ammonia levels. Patients developing signs of hepatobiliary disorders should be assessed early by a clinician knowledgeable in liver diseases in order to identify possible causative and contributory factors, and possible therapeutic and prophylactic interventions.

5.9 Aluminum Toxicity

Dextrose Injection contains no more than 25 mcg/L of aluminum. However, with prolonged parenteral administration in patients with renal impairment, the aluminum contained in Dextrose Injection may reach toxic levels. Preterm infants are at greater risk because their kidneys are immature, and they require large amounts of concomitant calcium and phosphate solutions that contain aluminum. Patients with renal impairment, including preterm infants, who receive parenteral levels of aluminum at greater than 4 to 5 mcg/kg/day, accumulate aluminum at levels associated with central nervous system (CNS) and bone toxicity. Tissue loading may occur at even lower rates of administration of total parenteral nutrition products [see Use in Specific Populations (8.4)].

5.10 Risk of Parenteral Nutrition Associated Liver Disease

Parenteral Nutrition Associated Liver Disease (PNALD) has been reported in patients who receive parenteral nutrition for extended periods of time, especially preterm infants, and can present as cholestasis or steatohepatitis. The exact etiology is not entirely clear and is likely multifactorial. If Dextrose Injection-treated patients develop abnormal liver function tests, consider discontinuation or dosage reduction.

5.11 Electrolyte Imbalance and Fluid Overload

Electrolyte deficits, particularly in serum potassium and phosphate, may occur during prolonged use of concentrated dextrose solutions.

Depending on the volume and rate of infusion, the intravenous administration of concentrated dextrose solutions can cause fluid and/or solute overloading resulting in dilution of serum electrolyte concentrations (including hypoosmotic hyponatremia), overhydration, congested states or pulmonary edema. The risk of dilutional states is inversely proportional to the electrolyte concentrations in the administered solution. The risk of solute overload causing congested states with peripheral and pulmonary edema is directly proportional to the electrolyte concentrations in the solution.

Monitor blood electrolyte levels, glucose, acid-base balance, correct fluid and electrolyte imbalances, and administer essential vitamins and minerals as needed. Monitor daily fluid balance. Additional monitoring is recommended for patients with water and electrolyte disturbances that could be aggravated by increased glucose and/or free water load. Patients at increased risk for developing hyponatremic encephalopathy include pediatric patients; elderly patients, women, in particular premenopausal women; patients with hypoxemia; and patients with underlying CNS disease [see Use in Specific Populations (8.4, 8.5)].

6 ADVERSE REACTIONS

The following adverse reactions associated with the use of Dextrose Injection were identified in clinical trials or postmarketing reports. Because these reactions were reported voluntarily from a population of uncertain size, it is not always possible to estimate their frequency, reliably, or to establish a causal relationship to drug exposure.

The following clinically significant adverse reactions are described elsewhere in the labeling:

- Pulmonary embolism due to pulmonary vascular precipitates [see Warnings and Precautions (5.1)]
- Hyperglycemia and hyperosmolar hyperglycemic state [see Warnings and Precautions (5.2)]
- Hypersensitivity reactions [see Warnings and Precautions (5.3)]
- Vein damage and thrombosis [see Warnings and Precautions (5.4)]
- Hyponatremia and hyponatremic encephalopathy [see Warnings and Precautions (5.5)]
- Risk of infections [see Warnings and Precautions (5.6)]
- Refeeding syndrome [see Warnings and Precautions (5.7)]
- Aluminum toxicity [see Warnings and Precautions (5.9)]
- Hepatobiliary disorders [see Warnings and Precautions (5.8)]
- Risk of parenteral nutrition associated liver disease [see Warnings and Precautions (5.10)]
- Electrolyte imbalance and fluid overload [see Warnings and Precautions (5.11)]

7 DRUG INTERACTIONS

7.1 Other Products that Affect Glycemic Control or Fluid and/or Electrolyte Balance

Dextrose Injection can affect glycemic control and fluid and/or electrolyte balance [see Warnings and Precautions (5.2, 5.5, 5.11)]. Monitor blood glucose concentrations, fluid balance, serum electrolyte concentrations and acid-base balance when using Dextrose Injection in patients treated with other substances that affect glycemic control, or fluid and/or electrolyte balance (such as diuretics and anti-epileptics).

8 USE IN SPECIFIC POPULATIONS

8.1 Pregnancy

Risk Summary

Appropriate administration of Dextrose Injection during pregnancy is not expected to cause adverse developmental outcomes, including congenital malformations. However, maternal hyperglycemia secondary to infusion of glucose-containing products at the time of delivery has been associated with adverse neonatal outcomes such as neonatal hypoglycemia. Malnutrition in pregnant women is associated with adverse maternal and fetal outcomes (see Clinical Considerations). Animal reproduction studies have not been conducted with injectable dextrose solutions.

The estimated background risk of major birth defects and miscarriage for the indicated population is unknown. All pregnancies have a background risk of birth defect, loss, or other adverse outcomes. In the U.S. general population, the estimated background risk of major birth defects and miscarriage in clinically recognized pregnancies is 2 to 4% and 15 to 20%, respectively.

Clinical Considerations

Disease-Associated Maternal and/or Embryo/Fetal Risk

Severe malnutrition in pregnant women is associated with preterm delivery, low birth weight, intrauterine growth restriction, congenital malformations and perinatal mortality. Parenteral nutrition should be considered if a pregnant woman’s nutritional requirements cannot be fulfilled by oral or enteral intake.

8.2 Lactation

Risk Summary

There are no data on the presence of dextrose in human milk, the effects on a breastfed infant, or the effects on milk production. The lack of clinical data during lactation precludes a clear determination of the risk of Dextrose Injection to an infant during lactation; therefore, the developmental and health benefits of breastfeeding should be considered along with the mother’s clinical need for Dextrose Injection and any potential adverse effects on the breastfed infant from Dextrose Injection or from the underlying maternal condition.

8.4 Pediatric Use

The safety profile of Dextrose Injection in pediatric patients is similar to adults.

Neonates, especially premature infants with low birth weight, are at increased risk of developing hypo- or hyperglycemia and therefore need close monitoring during treatment with intravenous glucose infusions to ensure adequate glycemic control in order to avoid potential long-term adverse effects.

Plasma electrolyte concentrations should be closely monitored in pediatric patients who may have impaired ability to regulate fluids and electrolytes. In very low birth weight infants, excessive or rapid administration of Dextrose Injection may result in increased serum osmolality and risk of intracerebral hemorrhage.

Because of immature renal function, preterm infants receiving prolonged treatment with dextrose injection, may be at risk of aluminum toxicity [see Warnings and Precautions (5.9)]. Patients, including pediatric patients, may be at risk for Parenteral Nutrition Associated Liver Disease (PNALD) [see Warnings and Precautions (5.10)].

Children (including neonates and older children) are at increased risk of developing hyponatremia as well as for developing hyponatremic encephalopathy.

8.5 Geriatric Use

Clinical studies of Dextrose Injection did not include sufficient numbers of subjects aged 65 and over to determine whether they respond differently from younger subjects. Elderly patients are at increased risk of developing hyponatremia as well as for developing hyponatremic encephalopathy [see Warnings and Precautions (5.5)]. Other reported clinical experience has not identified differences in responses between the elderly and younger patients. In general, dose selection for an elderly patient should be cautious, usually starting at the low end of the dosing range, reflecting the greater frequency of decreased hepatic, renal, or cardiac function, and of concomitant disease or other drug therapy.

This drug is known to be substantially excreted by the kidney, and the risk of toxic reactions to this drug may be greater in patients with impaired renal function. Because elderly patients are more likely to have decreased renal function, care should be taken in dose selection, and it may be useful to monitor renal function.

10 OVERDOSAGE

An increased infusion rate of Dextrose Injection or administration of a concentrated dextrose solution can cause hyperglycemia, hyperosmolality, and adverse effects on water and electrolyte balance [see Warnings and Precautions (5.2, 5.11)].

Severe hyperglycemia and severe dilutional hyponatremia, and their complications, can be fatal. Discontinue infusion and institute appropriate corrective measures such as administration of exogenous insulin.

Discontinue infusion and institute appropriate corrective measures in the event of overhydration or solute overload during therapy, with particular attention to CNS, respiratory and cardiovascular systems.

If over-exposure occurs, call your Poison Control Center at 1-800-222-1222 for current information on the management of poisoning or overdosage.

11 DESCRIPTION

Dextrose Injection 70%, USP is a clear, sterile, nonpyrogenic, hypertonic solution of Dextrose, USP in Water for Injection in a flexible plastic container as a Pharmacy Bulk Package. A Pharmacy Bulk Package is a container of a sterile preparation for parenteral use that contains many single doses. The contents are intended for use in a pharmacy admixture program. Dextrose Injection is not for direct intravenous infusion [see Dosage and Administration (2.1)].

The Pharmacy Bulk Package is designed to facilitate admixture or dilution to provide dextrose in various concentrations and is available in a 2000 mL size. See Table 1 for the content and characteristics of this solution.

The solution contains no bacteriostatic, antimicrobial agent or added buffer and is intended only for use following admixture or dilution. The pH range is 4.0 (3.2 to 6.5).

Water can permeate from inside the container into the overwrap but not in amounts sufficient to affect the solution significantly.

Table 1. Contents and Characteristics of Dextrose Injection 70%, USP
Strength | Fill Volume | Amount of Dextrose Hydrous, USP per container | kcal [Caloric value calculated on the basis of 3.4 kcal/g of dextrose, hydrous] per Container | Osmolarity (mOsmol per liter) (calc.)
Dextrose Injection 70%, USP (0.7 grams/mL) | 2000 mL | 1400 grams | 4760 | 3530

Dextrose, USP is chemically designated D-glucose, monohydrate (C6H12O6 • H2O), a hexose sugar freely soluble in water. The molecular weight of dextrose (D-glucose) monohydrate is 198.17. It has the following structural formula:

Water for Injection, USP is chemically designated H2O.

Dextrose Injection 70%, USP contains no more than 25 mcg/L of aluminum.

Dextrose is derived from corn.

12 CLINICAL PHARMACOLOGY

12.1 Mechanism of Action

Dextrose Injection is used to supplement nutrition by providing glucose parenterally. Dextrose is oxidized to carbon dioxide and water, yielding energy.

16 HOW SUPPLIED/STORAGE AND HANDLING

Dextrose Injection 70%, USP (0.7 grams/mL) is available in a Pharmacy Bulk Package flexible plastic container for intravenous administration after appropriate dilution [see Dosage and Administration (2.1)] and is available in the following size in Table 2 below.

Table 2
Product Description | Code | Volume | NDC
Dextrose Injection 70%, USP (0.7 grams/mL) | 2B0296 | 2000 mL | 0338-0719-06

Do not remove container from the overwrap until ready to use.

Store at room temperature (25°C /77°F).

Do not freeze.

Avoid excessive heat.

For storage of admixed solution, see Dosage and Administration (2.1).

17 PATIENT COUNSELING INFORMATION

Inform patients, caregivers, or home healthcare providers of the following risks of Dextrose Injection:

- Pulmonary embolism due to pulmonary vascular precipitates [see Warnings and Precautions (5.1)]
- Hyperglycemia and hyperosmolar hyperglycemic state [see Warnings and Precautions (5.2)]
- Hypersensitivity reactions [see Warnings and Precautions (5.3)]
- Vein damage and thrombosis [see Warnings and Precautions (5.4)]
- Hyponatremia [see Warnings and Precautions (5.5)]
- Risk of infections [see Warnings and Precautions (5.6)]
- Refeeding syndrome [see Warnings and Precautions (5.7)]
- Hepatobiliary disorders [see Warnings and Precautions (5.8)]
- Aluminum toxicity [see Warnings and Precautions (5.9)]
- Risk of parenteral nutrition associated liver disease [see Warnings and Precautions (5.10)]
- Electrolyte imbalance and fluid overload [see Warnings and Precautions (5.11)]

Manufactured by, Packed by, Distributed by:

Baxter Healthcare Corporation
Deerfield, IL 60015 USA

07-19-73-116

Baxter and Viaflex are trademarks of Baxter International Inc.

PACKAGE/LABEL PRINCIPAL DISPLAY PANEL

Container Label

Container Label

LOT
EXP

2B0296
NDC 0338-0719-06

2000 mL
DIN 02014874

DEXTROSE
Injection USP

70%

Pharmacy Bulk Package
Not For Direct Infusion
Must Be Diluted

Rx Only

EACH 100 mL CONTAINS 70 g DEXTROSE HYDROUS USP
IN WATER FOR INJECTION USP

pH 4.0 (3.2 to 6.5) SPECIFIC GRAVITY 1.24 (CALC)

HYPERTONIC OSMOLARITY 3530 mOsmol/L (CALC)

STERILE NONPYROGENIC

CONTAINS NO MORE THAN 25 µg/L OF ALUMINUM

COLOR VARIATION FROM LIGHT YELLOW TO AMBER IS NORMAL
AND DOES NOT ALTER EFFICACY

DOSAGE AND ADMINISTRATION SEE PACKAGE INSERT

CAUTION DO NOT USE UNLESS SOLUTION IS CLEAR CLOSURE
IS INTACT AND CONTAINER IS UNDAMAGED

CHECK FOR MINUTE LEAKS BY SQUEEZING FIRMLY
IF LEAKS ARE FOUND DISCARD AS STERILITY MAY BE IMPAIRED

AFFIX ACCOMPANYING LABEL FOR DATE AND TIME OF ENTRY

WITHIN 4 HOURS AFTER INITIAL ENTRY DISCARD CONTAINER
AND UNUSED CONTENTS

STORE UNIT IN MOISTURE BARRIER OVERWRAP AT
ROOM TEMPERATURE (25°C/77°F) UNTIL READY TO USE
AVOID EXCESSIVE HEAT PROTECT FROM FREEZING

VIAFLEX CONTAINER

PL 146 PLASTIC

Baxter Logo

BAXTER HEALTHCARE CORPORATION
DEERFIELD IL 60015 USA

DISTRIBUTED IN CANADA BY
BAXTER CORPORATION
Mississauga, ON L5N 0C2

MADE IN USA

BAXTER PL 146
AND VIAFLEX ARE
TRADEMARKS OF BAXTER
INTERNATIONAL INC

70%